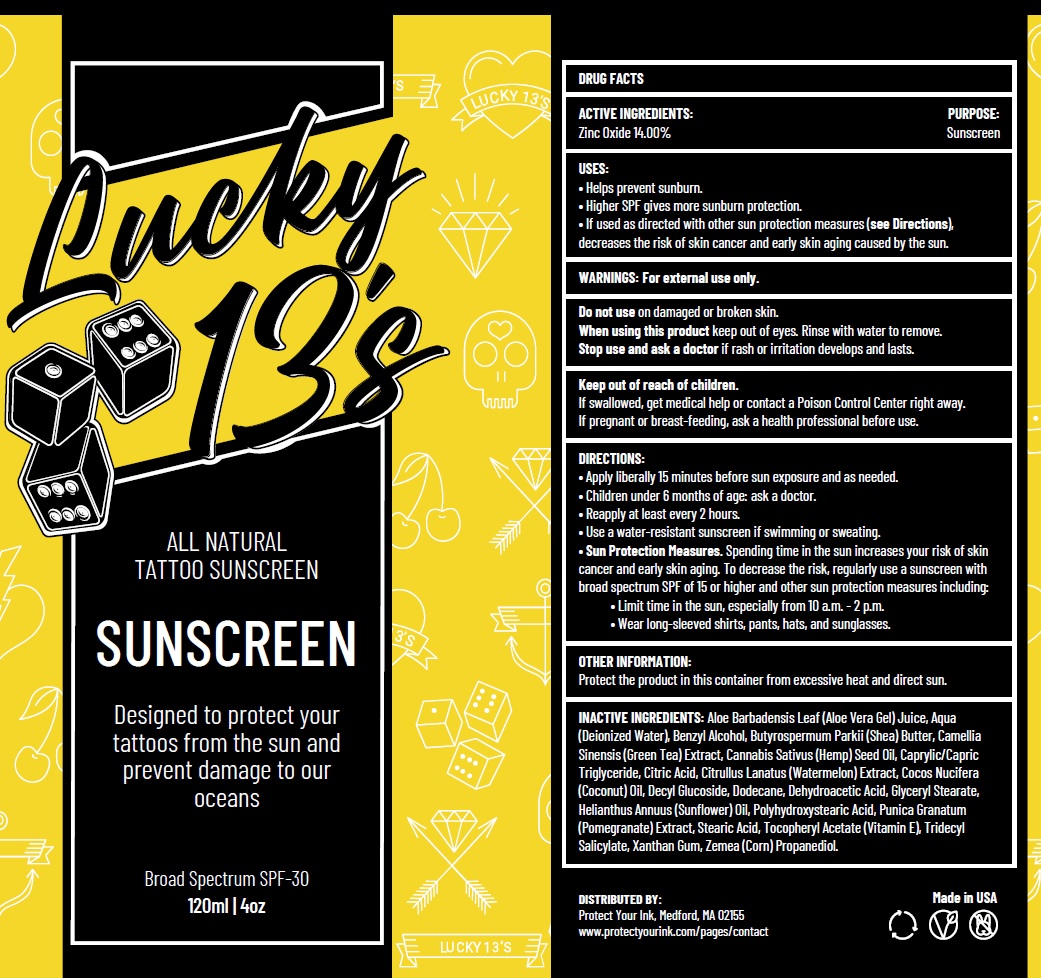 DRUG LABEL: LUCKY 13s ALL NATURAL TATTOO SUNSCREEN SPF-30
NDC: 82459-249 | Form: CREAM
Manufacturer: SALES BRAIN HOLDINGS LLC
Category: otc | Type: HUMAN OTC DRUG LABEL
Date: 20231111

ACTIVE INGREDIENTS: ZINC OXIDE 140 mg/1 mL
INACTIVE INGREDIENTS: ALOE VERA LEAF; WATER; BENZYL ALCOHOL; SHEA BUTTER; GREEN TEA LEAF; HEMP; MEDIUM-CHAIN TRIGLYCERIDES; CITRIC ACID MONOHYDRATE; WATERMELON; COCONUT OIL; DECYL GLUCOSIDE; DODECANE; DEHYDROACETIC ACID; GLYCERYL MONOSTEARATE; HELIANTHUS ANNUUS FLOWERING TOP; PUNICA GRANATUM ROOT BARK; STEARIC ACID; .ALPHA.-TOCOPHEROL ACETATE; TRIDECYL SALICYLATE; XANTHAN GUM; CORN

LUCKY 13s ALL NATURAL TATTOO SUNSCREEN SPF-30

ACTIVE INGREDIENTS:

Zinc Oxide 14.00%

PURPOSE:

Sunscreen

USES:

• Helps prevent sunburn. • Higher SPF gives more sunburn protection. • If used as directed with other sun protection measures (see Directions), decreases the risk of skin cancer and early skin aging caused by the sun.

WARNINGS:

For external use only.

Do not use

on damaged or broken skin.

When using this product

keep out of eyes. Rinse with water to remove.

Stop use and ask a doctor

if rash or irritation develops and lasts.

Keep out of reach of children.

If swallowed, get medical help or contact a Poison Control Center right away.

If pregnant or breast-feeding,

ask a health professional before use.

DIRECTIONS:

• Apply liberally 15 minutes before sun exposure and as needed. • Children under 6 months of age: ask a doctor. • Reapply at least every 2 hours. • Use a water-resistant sunscreen if swimming or sweating. • Spending time in the sun increases your risk of skin cancer and early skin aging. To decrease the risk, regularly use a sunscreen with broad spectrum SPF of 15 or higher and other sun protection measures including: • Limit time in the sun, especially from 10 a.m. - 2 p.m. • Wear long-sleeved shirts, pants, hats, and sunglasses.
Sun Protection Measures.

OTHER INFORMATION:

Protect the product in this container from excessive heat and direct sun.

INACTIVE INGREDIENTS:

Aloe Barbadensis Leaf (Aloe Vera Gel) Juice, Aqua (Deionized Water), Benzyl Alcohol, Butyrospermum Parkii (Shea) Butter, Camellia Sinensis (Green Tea) Extract, Cannabis Sativus (Hemp) Seed Oil, Caprylic/Capric Triglyceride, Citric Acid, Citrullus Lanatus (Watermelon) Extract, Cocos Nucifera (Coconut) Oil, Decyl Glucoside, Dodecane, Dehydroacetic Acid, Glyceryl Stearate, Helianthus Annuus (Sunflower) Oil, Polyhydroxystearic Acid, Punica Granatum (Pomegranate) Extract, Stearic Acid, Tocopheryl Acetate (Vitamin E), Tridecyl Salicylate, Xanthan Gum, Zemea (Corn) Propanediol.